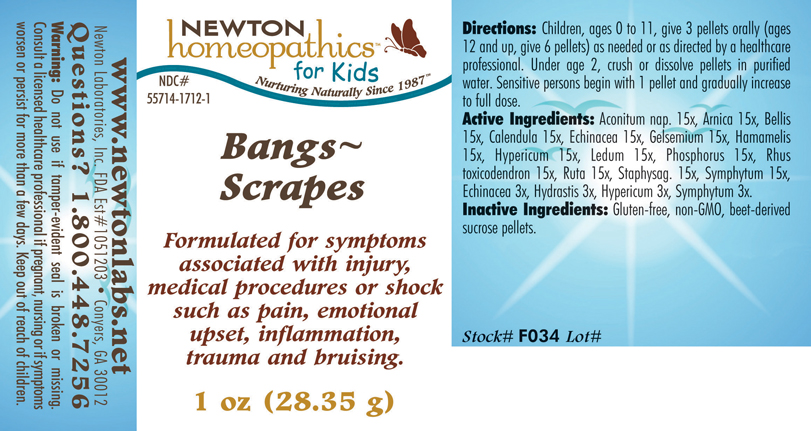 DRUG LABEL: Bangs Scrapes 
NDC: 55714-1712 | Form: PELLET
Manufacturer: Newton Laboratories, Inc.
Category: homeopathic | Type: HUMAN OTC DRUG LABEL
Date: 20110301

ACTIVE INGREDIENTS: Aconitum Napellus 15 [hp_X]/1 g; Arnica Montana Root 15 [hp_X]/1 g; Bellis Perennis 15 [hp_X]/1 g; Calendula Officinalis Flowering Top 15 [hp_X]/1 g; Echinacea, Unspecified 15 [hp_X]/1 g; Gelsemium Sempervirens Root 15 [hp_X]/1 g; Hamamelis Virginiana Root Bark/stem Bark 15 [hp_X]/1 g; Hypericum Perforatum 15 [hp_X]/1 g; Ledum Palustre Twig 15 [hp_X]/1 g; Phosphorus 15 [hp_X]/1 g; Toxicodendron Pubescens Leaf 15 [hp_X]/1 g; Ruta Graveolens Flowering Top 15 [hp_X]/1 g; Delphinium Staphisagria Seed 15 [hp_X]/1 g; Comfrey Root 15 [hp_X]/1 g; Goldenseal 3 [hp_X]/1 g
INACTIVE INGREDIENTS: Sucrose

Bangs - Scrapes

INDICATIONS & USAGE SECTION

Bangs - Scrapes Formulated for symptoms associated with injury, medical procedures or shock such as pain, emotional upset, inflammation, trauma and bruising.

DOSAGE & ADMINISTRATION SECTION

Directions: Children, ages 0 to 11, give 3 pellets orally (ages 12 and up, give 6 pellets) as needed or as directed by a healthcare professional. Unde age 2, crush or dissolve pellets in purified water. Sensitive persons begin with 1 pellet and gradually increase to full dose.

OTC - ACTIVE INGREDIENT SECTION

Aconitum nap. 15x, Arnica 15x, Bellis15x, Calendula 15x, Echinacea 15x, Gelsemium 15x, Hamamelis 15x, Hypericum 15x, Ledum 15x, Phosphorus 15x, Rhus toxicodendron 15x, Ruta 15x, Staphysag. 15x, Symphytum 15x, Echinacea 3x, Hydrastis 3x, Hypericum 3x, Symphytum 3x.

OTC - PURPOSE SECTION

Formulated for symptoms associated with injury, medical procedures or shock such as pain, emotional upset, inflammation, trauma and bruising.

INACTIVE INGREDIENT SECTION

Inactive Ingredients: Gluten-free, non-GMO, beet-derived sucrose pellets.

QUESTIONS SECTION

www.newtonlabs.net Newton Laboratories, Inc. FDA Est # 1051203 - Conyers, GA 30012
Questions? 1.800.448.7256

WARNINGS SECTION

Warning: Do not use if tamper - evident seal is broken or missing. Consult a licensed healthcare professional if pregnant, nursing or if symptoms worsen or persist for more than a few days. Keep out of reach of children.

OTC - PREGNANCY OR BREAST FEEDING SECTION

Consult a licensed healthcare professional if pregnant, nursing or if symptoms worsen or persist for more than a few days.

OTC - KEEP OUT OF REACH OF CHILDREN SECTION

Keep out of reach of children.